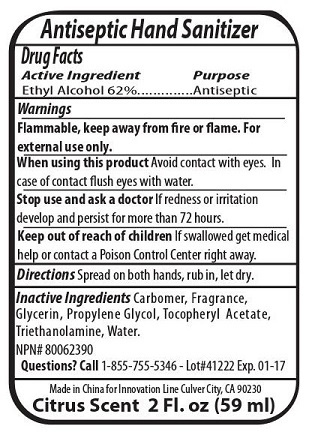 DRUG LABEL: Antiseptic Hand Sanitizer
NDC: 76138-113 | Form: GEL
Manufacturer: Innovation Specialties Inc
Category: otc | Type: HUMAN OTC DRUG LABEL
Date: 20240710

ACTIVE INGREDIENTS: ALCOHOL 62 mL/100 mL
INACTIVE INGREDIENTS: CARBOMER HOMOPOLYMER, UNSPECIFIED TYPE; GLYCERIN; PROPYLENE GLYCOL; .ALPHA.-TOCOPHEROL ACETATE; TROLAMINE; WATER

Antiseptic Hand Sanitizer

Active Ingredient

Ethyl Alcohol 62%

Purpose

Antiseptic

KEEP OUT OF REACH OF CHILDREN

Keep out of reach of childrenIf swallowed get medical help or contact a Poison Control Center right away.

Use

To help clean hands

Warnings

Flammable, keep away from fire or flame. For external use only.

When using this productAvoid contact with eyes. In case of contact flush eyes with water.

Stop use and ask a doctorIf redness or irritation develop and persist for more than 72 hours.

Directions

Spread on both hands, rub in, let dry.

Inactive Ingredients

Carbomer, Fragrance, Glycerin, Propylene Glycol, Tocopheryl Acetate, Triethanolamine, Water.

Questions?

Call1-855-755-5346

Made in China for Innovation Line Culver City, CA 90230

Citrus Scent